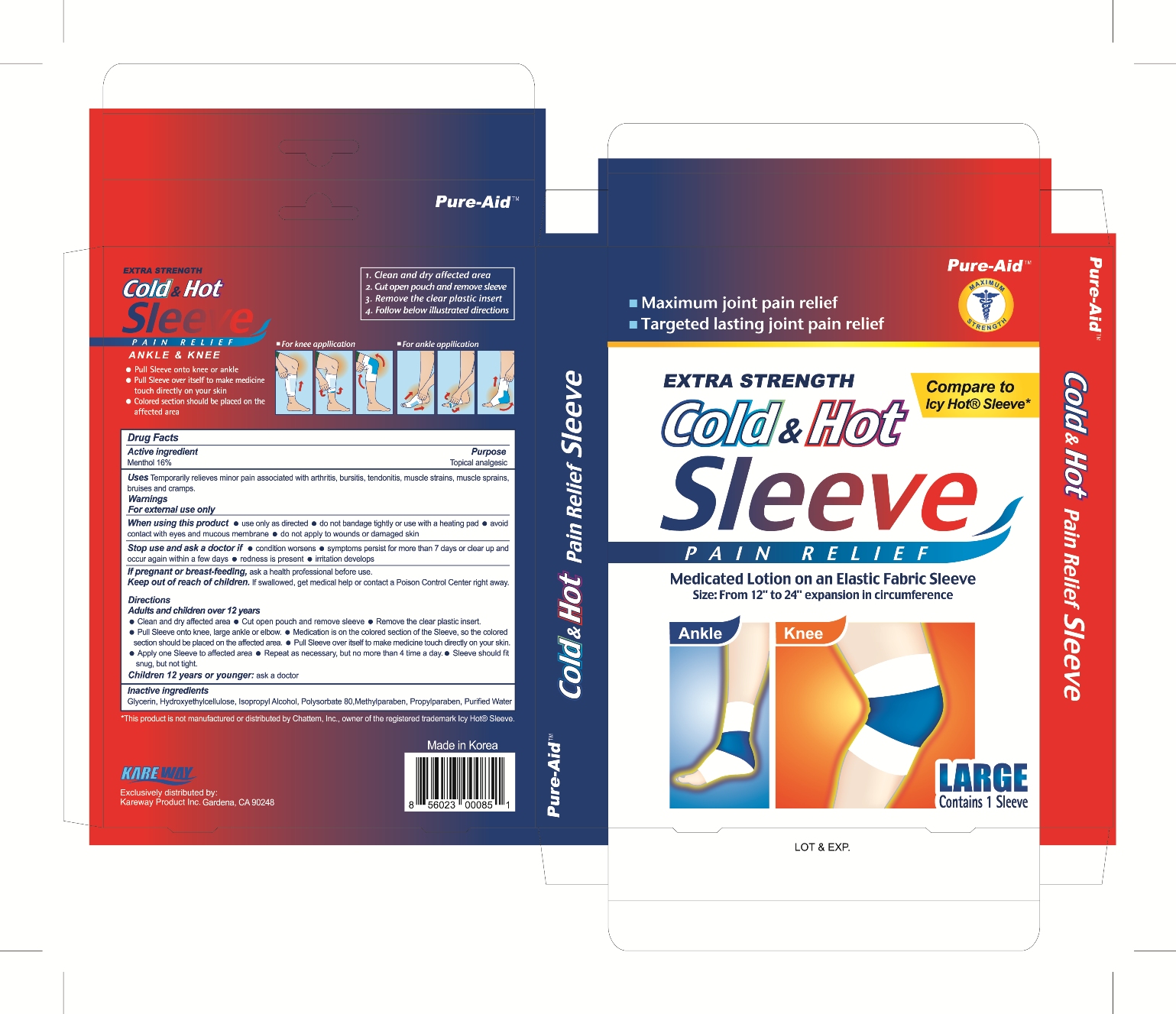 DRUG LABEL: Cold and Hot Pain Relief Sleeve
NDC: 67510-0085 | Form: PATCH
Manufacturer: Kareway Product, Inc.
Category: otc | Type: HUMAN OTC DRUG LABEL
Date: 20200904

ACTIVE INGREDIENTS: MENTHOL 400 mg/1 1
INACTIVE INGREDIENTS: GLYCERIN; ISOPROPYL ALCOHOL; POLYSORBATE 80; METHYLPARABEN; PROPYLPARABEN; WATER

Pure-Aid Cold & Hot Sleeve

Active ingredient

Menthol 16%

Purpose

Topical analgesic

Uses

Temporarily relieves minor pain associated with arthritis, bursitis, tendonitis, muscle strains, muscle sprains, bruises and cramps.

Warnings

For external use only

When using this product

- use only as directed
- do not bandage tightly or use with a heating pad
- avoid contact with eyes and mucous membrane
- do not apply to wounds or damaged skin

Stop use and ask a doctor if

- condition worsens
- symptoms persist for more than 7 days or clear up and occur again within a few days
- redness is present
- irritation develops

If pregnant or breast-feeding,

ask a health professional before use.

Keep out of reach of children.

If swallowed, get medical help or contact a Poison Control Center right away.

Directions

Adults and children over 12 years

- Clean and dry affected area.
- Cut open pouch and remove Sleeve.
- Remove the clear plastic insert.
- Pull Sleeve onto knee, large ankle or elbow.
- Medication is on the colored section of the Sleeve, so the colored section should be placed on the affected area.
- Pull Sleeve over itself to make medicine touch directly on your skin.
- Apply one Sleeve to affected area.
- Repeat as necessary , but no more than 4 times a day.
- Sleeve should fit snug, but not tight.

Children 12 years or younger:

- ask a doctor

Inactive ingredients

Glycerin, Hydroxyethylcellulose, Isopropyl Alcohol, Polysorbate 80, Methylparaben, Propylparaben, Purified Water